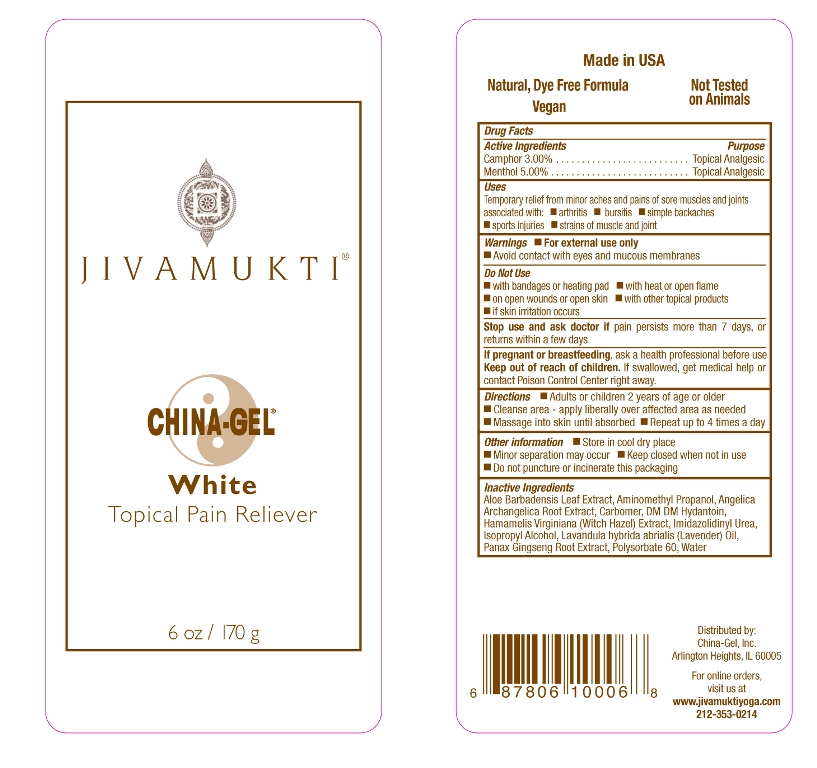 DRUG LABEL: Jivamukti
NDC: 76305-401 | Form: CREAM
Manufacturer: China-Gel, Inc.
Category: otc | Type: HUMAN OTC DRUG LABEL
Date: 20160208

ACTIVE INGREDIENTS: MENTHOL 5 g/100 g; CAMPHOR (NATURAL) 3 g/100 g
INACTIVE INGREDIENTS: CARBOMER HOMOPOLYMER TYPE C; POLYSORBATE 60; ALOE VERA LEAF; AMINOMETHYLPROPANOL; ANGELICA ARCHANGELICA ROOT; DMDM HYDANTOIN; HAMAMELIS VIRGINIANA TOP; IMIDUREA; ISOPROPYL ALCOHOL; LAVANDIN OIL; ASIAN GINSENG; WATER

Drug Facts

Active Ingredients

Camphor 3.00%

Menthol 5.00%

Purpose

Topical Analgesic

Uses

Temporary relief from minor aches and pains of sore uscles and joints associated with:

- arthritis
- bursitis
- simple backaches
- sports injuries
- strains of muscle and joint

Warnings

- For external use only
- Avoid contact with eyes and mucous membranes

Do Not Use

- with bandages or heating pad
- with heat or open flame
- on open wounds or open skin
- with other topical products
- if skin irritation occurs

Stop use and ask a doctor if

pain persists more than 7 days, or returns within a few days

If pregnant or breastfeeding,

ask a health professional before use

Keep out of reach of children.

If swallowed, get medical help or contact Poison Control Center right away.

Directions

- Adults or children 2 years of age or older
- Cleanse area - apply liberally over affected area as needed
- Massage into skin until absorbed
- Repeat up to 4 times a day

Other information

- Store in cool dry place
- Minor separation may occur
- Keep closed when not in use
- Do not puncture of incinerate this packaging

Inactive Ingredients

Aloe Barbadensis Leaf Extract, Aminomethyl Propanol, Angelica Archangelica Root Extract, Carbomer, DM DM Hydantoin, Hamamelis Virginiana (Witch Hazel) Extract, Imidazolidinyl Urea, Isopropyl Alcohol, Lavandula hybrida abrialis (Lavender) oil, Panax Ginseng Root Extract, Polysorbate 60, Water

Distributed by:

China-Gel, Inc.

Arlington Heights, IL 60005

For online orders, visit us at

www.jivamuktiyoga.com

212-353-0214

Natural, Dye Free Formula

Made in the USA

Vegan

Not Tested on Animals

Principal Display Panel

JIVAMUKTI®

CHINA-GEL®

White

Topical Pain Reliever

6 oz/170 g